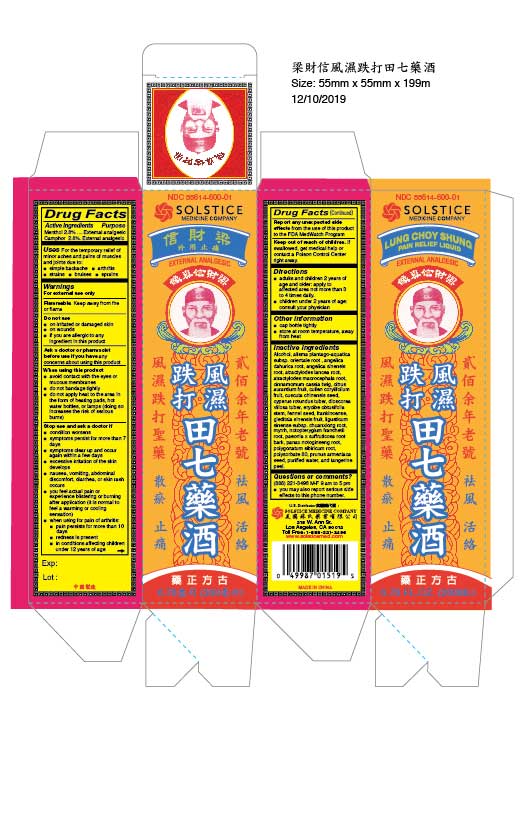 DRUG LABEL: Lung Choy Shung Pain Relief Liquid
NDC: 55614-600 | Form: LINIMENT
Manufacturer: MADISON ONE ACME INC
Category: otc | Type: HUMAN OTC DRUG LABEL
Date: 20251110

ACTIVE INGREDIENTS: MENTHOL 2.8 g/100 mL; CAMPHOR (SYNTHETIC) 2.8 g/100 mL
INACTIVE INGREDIENTS: ALCOHOL; ALISMA PLANTAGO-AQUATICA SUBSP. ORIENTALE ROOT; ANGELICA DAHURICA ROOT; ANGELICA SINENSIS ROOT; ATRACTYLODES LANCEA ROOT; ATRACTYLODES MACROCEPHALA ROOT; CINNAMOMUM CASSIA TWIG; CITRUS AURANTIUM FRUIT; CULLEN CORYLIFOLIUM FRUIT; CUSCUTA CHINENSIS SEED; CYPERUS ROTUNDUS TUBER; DIOSCOREA VILLOSA TUBER; ERYCIBE OBTUSIFOLIA STEM; FENNEL SEED; FRANKINCENSE; GLEDITSIA SINENSIS FRUIT; LIGUSTICUM SINENSE SUBSP. CHUANXIONG ROOT; MYRRH; INCISED NOTOPTERYGIUM RHIZOME OR ROOT (NOTOPTERYGIUM FRANCHETII); PAEONIA X SUFFRUTICOSA ROOT BARK; PANAX NOTOGINSENG ROOT; POLYGONATUM SIBIRICUM ROOT; POLYSORBATE 80; PRUNUS ARMENIACA SEED; WATER; TANGERINE PEEL

Drug Facts

Active ingredient
Menthol 2.8%
Camphor 2.8%

Purpose
External analgesic
External analgesic

Uses
For the temporary relief of minor aches and pains of muscles and joints due to:
simple backache
arthritis
strains
bruises
sprains

Warnings
For external use only

Flammable:Keep away from fire or flame.

Do not use
on irritated or damaged skin
on wounds
if you are allergic to any ingredient in this product

Ask a doctor or pharmacist before use if you have
any concerns about using this product

When using this product
avoid contact with the eyes or mucous membranes do not bandage tightly
do not apply heat to the area in the form of heating pads, hot water bottles, or lamps (doing so increases the risk of serious burns)

Stop use and ask a doctor if
condition worsens
symptoms persist for more than 7 days
symptoms clear up and occur again within a few days
excessive irritation of the skin develops
nausea, vomiting, abdominal discomfort, diarrhea, or skin rash occurs
you feel actual pain or experience blistering or burning after application (it is normal to feel a warming or cooling sensation)
when using for pain of arthritis:
pain persists for more than 10 days
redness is present
in conditions affecting children under 12 years of age

ADVERSE REACTIONS

Report any unexpected side effectsfrom the use of this product to the FDA MedWatch Program

Keep out of reach of children.If swallowed, get medical help or contact a Poison Control Center right away.

Directions
adults and children 2 years of age and older: apply to affected area not more than 3 to 4 times daily.
children under 2 years of age: consult your physician

Other information
cap bottle tightly
store at room temperature, away from heat

Inactive ingredients
Alcohol, alisma plantago-aquatica subsp. orientale root , angelica dahurica root, angelica sinensis root, atractylodes lancea root, atractylodes macrocephala root, cinnamomum cassia twig, citrus aurantium fruit, cullen corylifolium fruit, cuscuta chinensis seed, cyperus rotundus tuber, dioscorea villosa tuber, erycibe obtusifolia stem, fennel seed, frankincense, gleditsia sinensis fruit, ligusticum sinense subsp. chuanxiong root, myrrh, notopterygium franchetii root, paeonia x suffruticosa root bark, panax notoginseng root, polygonatum sibiricum root, polysorbate 80, prunus armeniaca seed, purified water, and tangerine peel.

Questions or comments?(888) 221-3496 M-F 9 am to 5 pm
you may also report serious side effects to this phone number

PACKAGE LABEL

Lung Choy Shung Pain Relief Liquid
External Analgesic
NDC 55614-600-01
Menthol and Camphor
6.76 fl oz (200 mL)